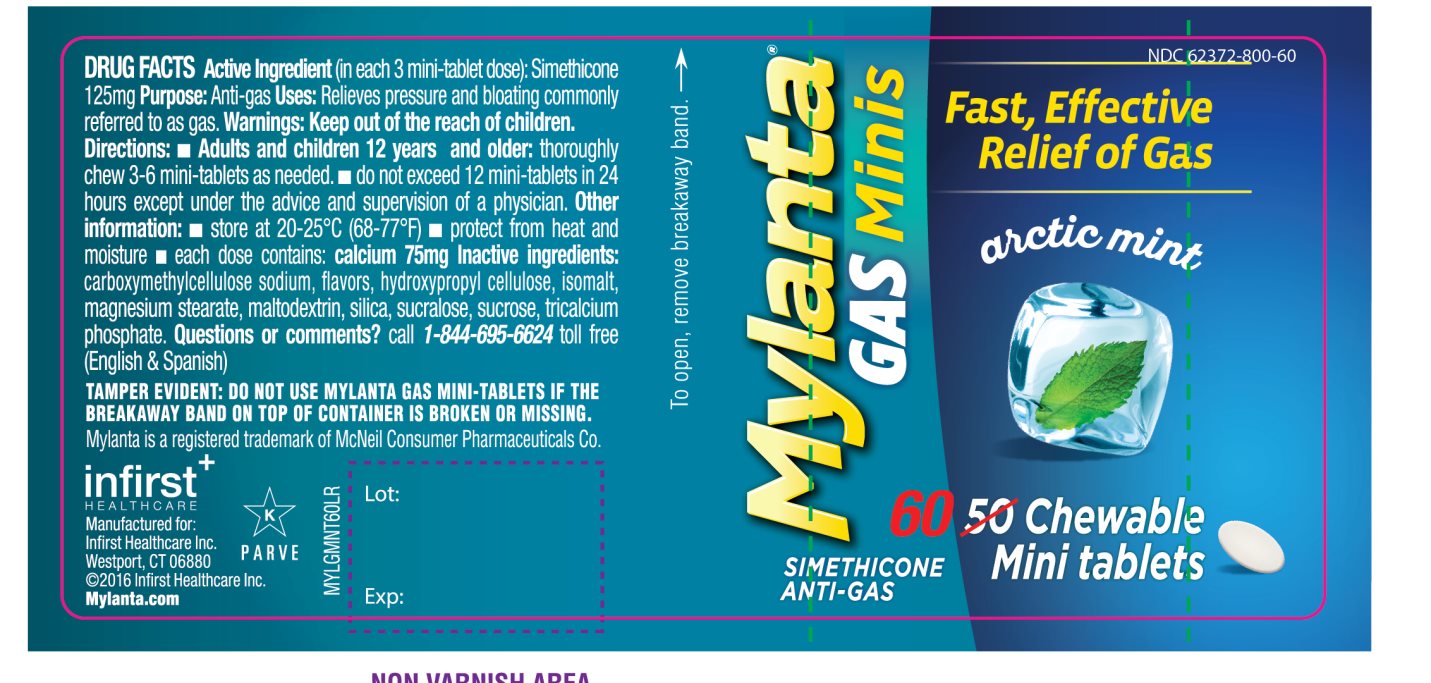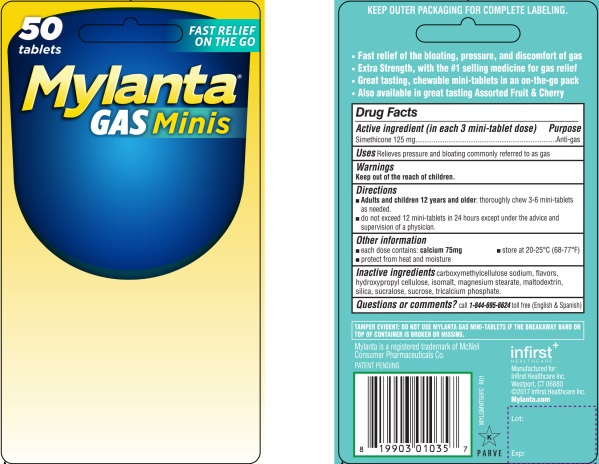 DRUG LABEL: Mylanta Gas Minis Mint Flavor
NDC: 62372-800 | Form: TABLET, CHEWABLE
Manufacturer: Infirst Healthcare Inc.
Category: otc | Type: HUMAN OTC DRUG LABEL
Date: 20231204

ACTIVE INGREDIENTS: DIMETHICONE 125 mg/1 1
INACTIVE INGREDIENTS: CARBOXYMETHYLCELLULOSE SODIUM, UNSPECIFIED FORM; HYDROXYPROPYL CELLULOSE (1600000 WAMW); ISOMALT; MAGNESIUM STEARATE; MALTODEXTRIN; SILICON DIOXIDE; SUCRALOSE; SUCROSE; TRICALCIUM PHOSPHATE

Mylanta Gas Minis Chewable Tablets Mint

Active ingredient (in each 3 mini -tablet dose)

Simethicone 125 mg

Purpose

Anti-gas

Uses

Relieves pressure and bloating commonly referred to as gas

Warnings

Keep out of the reach of children.

Directions

- Adults and children 12 years and older: thoroughly chew 3-6 mini-tablets as needed.
- do not exceed 12 mini-tablets in 24 hours except under the advice and supervision of a physician.

Other information

- each dose contains: calcium 75 mg
- protect from heat and moisture
- store at 20-25° C (68-77° F)

Inactive ingredients

carboxymethylcellulose sodium, flavors, hydroxypropyl cellulose, isomalt, magnesium stearate, maltodextrin, silica, sucralose, sucrose, tricalcium phosphate

Questions or comments?

call 1-844-695-6624toll free (English & Spanish)

Principal Display Panel

FREE 20% MORE

CONVENIENT POCKET PACK

FAST RELIEF ON THE GO

Mylanta®

GAS Minis

- Fast relief of the bloating , pressure, and discomfort of gas
- Extra Strength, with the #1 selling medicine for gas relief
- Great tasting ,chewable mini-tablets in an on-the-go pack
- Also available in great tasting Assorted Fruit & Cherry

TAMPER EVIDENT: DO NOT USE MYLANTA GAS MINI-TABLETS IF THE BREAKAWAY BAND ON TOP OF CONTAINER IS BROKEN OR MISSING.

1. Mylanta is a registered trademark of McNeil Consumer Pharmaceuticals Co.

Patent pending

infirst^+

HEALTHCARE

Manufactured for:

Infirst Healthcare Inc.

Westport, CT 06880

©2016 Infirst Healthcare Inc.

Mylanta.com

KEEP OUTER PACKAGING FOR COMPLETE LABELING

Package Label for 50 Chewable Tablets